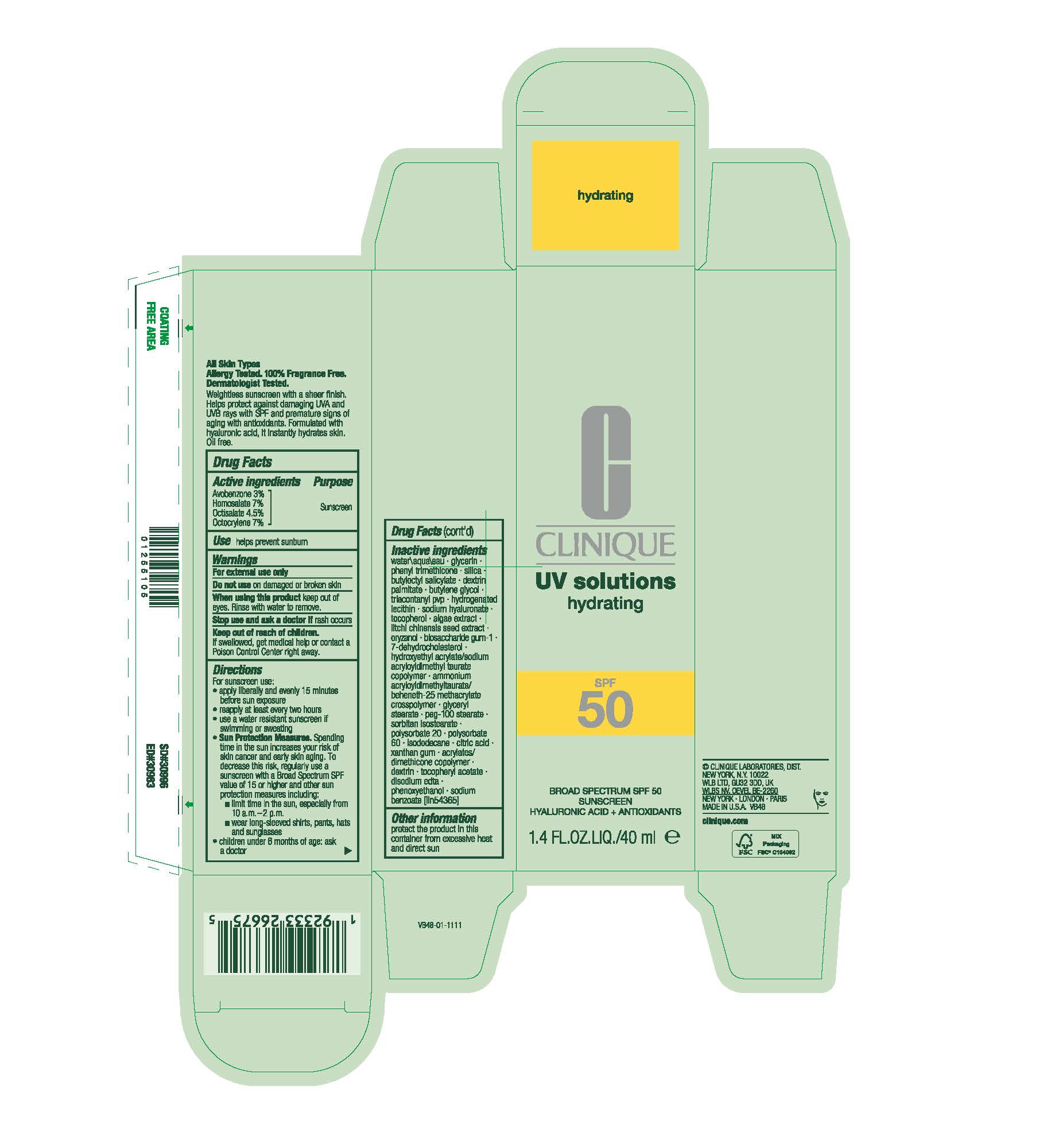 DRUG LABEL: UV SOLUTIONS HYDRATING BROAD SPECTRUM SPF 50
NDC: 49527-224 | Form: CREAM
Manufacturer: CLINIQUE LABORATORIES LLC
Category: otc | Type: HUMAN OTC DRUG LABEL
Date: 20260201

ACTIVE INGREDIENTS: AVOBENZONE 30 mg/1 mL; OCTISALATE 45 mg/1 mL; OCTOCRYLENE 70 mg/1 mL; HOMOSALATE 70 mg/1 mL
INACTIVE INGREDIENTS: SODIUM BENZOATE; BIOSACCHARIDE GUM-1; 7-DEHYDROCHOLESTEROL; GLYCERYL STEARATE; POLYSORBATE 20; DEXTRIN PALMITATE (CORN; 20000 MW); TOCOPHEROL; LITCHI CHINENSIS SEED; XANTHAN GUM; PHENYL TRIMETHICONE; HYDROXYETHYL ACRYLATE/SODIUM ACRYLOYLDIMETHYL TAURATE COPOLYMER (45000 MPA.S AT 1%); PEG-100 STEARATE; WATER; AMMONIUM ACRYLOYLDIMETHYLTAURATE/BEHENETH-25 METHACRYLATE CROSSPOLYMER (52000 MPA.S); SODIUM HYALURONATE; ALPHA-TOCOPHEROL ACETATE; BUTYLOCTYL SALICYLATE; SORBITAN ISOSTEARATE; POLYSORBATE 60; GLYCERIN; TRIACONTANYL PVP; PORPHYRIDIUM PURPUREUM; ICODEXTRIN; EDETATE DISODIUM ANHYDROUS; ORYZANOL; HYDROGENATED SOYBEAN LECITHIN; PHENOXYETHANOL; BUTYLENE GLYCOL; SILICA; ISODODECANE; CITRIC ACID

UV SOLUTIONS HYDRATING BROAD SPECTRUM SPF 50

Active ingredietns

Avobenzone 3%

Homosalate 7%

Octisalate 4.5%

Octocrylene 7%

Purpose

Sunscreen

Use

helps prevent sunburn

WARNINGS

For external use only

Do not use

on damaged or broken skin

When using this product

Keep out of eyes. Rinse with water to remove.

Stop use and ask a doctor if

rash occurs

Keep out of reach of children

If swallowed, get medical help or contact a Poison Control Center right away.

Directions

- For sunscreen use:
- apply liberally and evenly 15 minutes before sun exposure
- reapply at least every two hours
- use a water resistant sunscreen if swimming or sweating
- Sun Protection Measures. Spending time in the sun increases your risk of skin cancer and early skin aging. To decrease this risk, regularly use a sunscreen with a Broad Spectrum SPF value of 15 or higher and other sun protection measures including:
  - limit time in the sun, especially from 10 a.m.–2 p.m.
  - wear long-sleeved shirts, pants, hats and sunglasses
- children under 6 months of age: ask a doctor

Inactive ingredients

water\aqua\eau • glycerin • phenyl trimethicone • silica • butyloctyl salicylate • dextrin palmitate • butylene glycol • triacontanyl pvp • hydrogenated lecithin • sodium hyaluronate • tocopherol • algae extract • litchi chinensis seed extract • oryzanol • biosaccharide gum-1 • 7-dehydrocholesterol • hydroxyethyl acrylate/sodium acryloyldimethyl taurate copolymer • ammonium acryloyldimethyltaurate/beheneth-25 methacrylate crosspolymer • glyceryl stearate • peg-100 stearate • sorbitan isostearate • polysorbate 20 • polysorbate 60 • isododecane • citric acid • xanthan gum • acrylates/dimethicone copolymer • dextrin • tocopheryl acetate • disodium edta • phenoxyethanol • sodium benzoate [iln54365]

Other information

protect the product in this container from excessive heat and direct sun

PACKAGE LABEL

CLINIQUE
UV solutions
hydrating
SPF 50
BROAD SPECTRUM SPF 50
SUNSCREEN
HYALURONIC ACID+ ANTIOXIDANTS
1.4 FL.OZ.LIQ./40 ml e